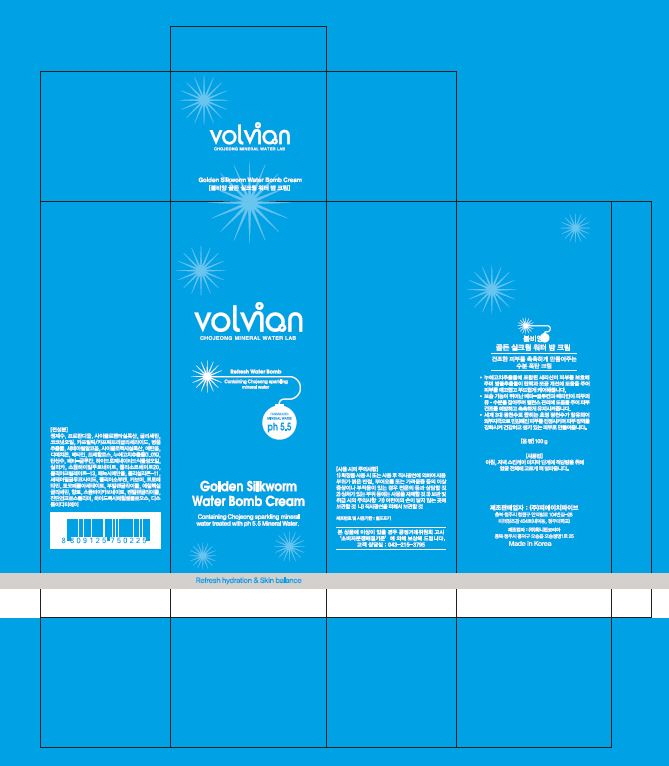 DRUG LABEL: VOLVIAN GOLDEN SILKWORM WATER BOMB
NDC: 71461-0001 | Form: CREAM
Manufacturer: ph5
Category: otc | Type: HUMAN OTC DRUG LABEL
Date: 20170620

ACTIVE INGREDIENTS: GLYCERIN 4 g/100 g
INACTIVE INGREDIENTS: WATER; BUTYLENE GLYCOL

Drug Facts

ACTIVE INGREDIENT

Glycerin

INACTIVE INGREDIENT

Water, Propanediol, Beta-Glucan, Betaine, etc.

PURPOSE

Skin Protectant

keep out of reach of the children

INDICATIONS AND USAGE

At the last of skincare step, apply proper amount to skin and spread evenly.

WARNINGS

1. If the following symptoms occur after product use, stop using the product immediately and consult a dermatologist (continuous use can exacerbate the symptoms).
1) Occurrence of red spots, swelling, itchiness, and other skin irritation
2) If the symptoms above occur after the application area is exposed to direct sunlight
2. Do not use on open wounds, eczema, and other skin irritations
3. Precaution for Storage and Handling
1) Close the lid after use
2) Keep out of reach of infants and children
3) Do not to store in a place with high/low temperature and exposed to direct sunlight

4. Use as avoiding eye areas.

DOSAGE AND ADMINISTRATION

for external use only